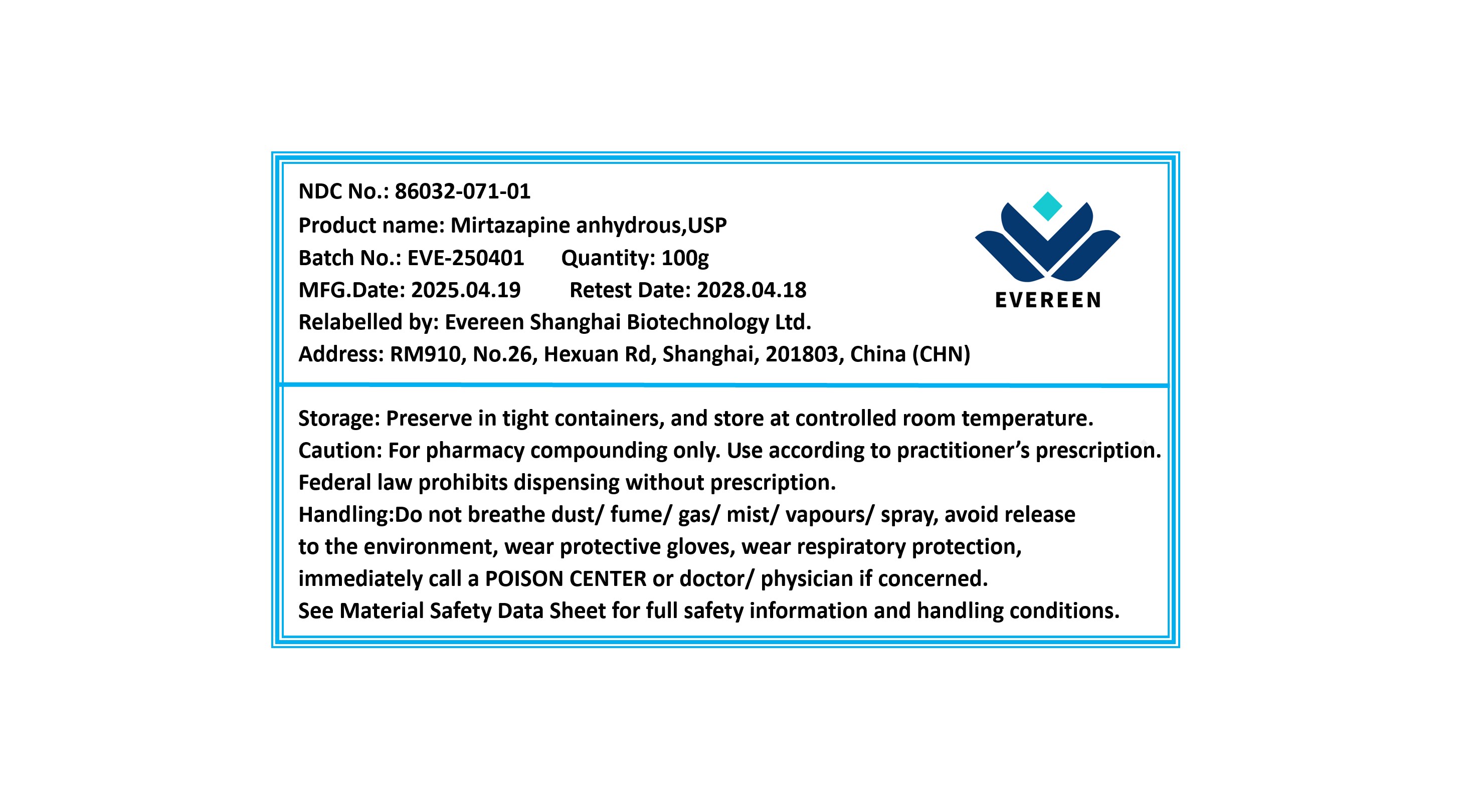 DRUG LABEL: Mirtazapine anhydrous
NDC: 86032-071 | Form: POWDER
Manufacturer: Evereen Shanghai Biotechnology Ltd.
Category: other | Type: BULK INGREDIENT - ANIMAL DRUG
Date: 20260203

ACTIVE INGREDIENTS: MIRTAZAPINE 1 g/1 g

Mirtazapine Anhydrous